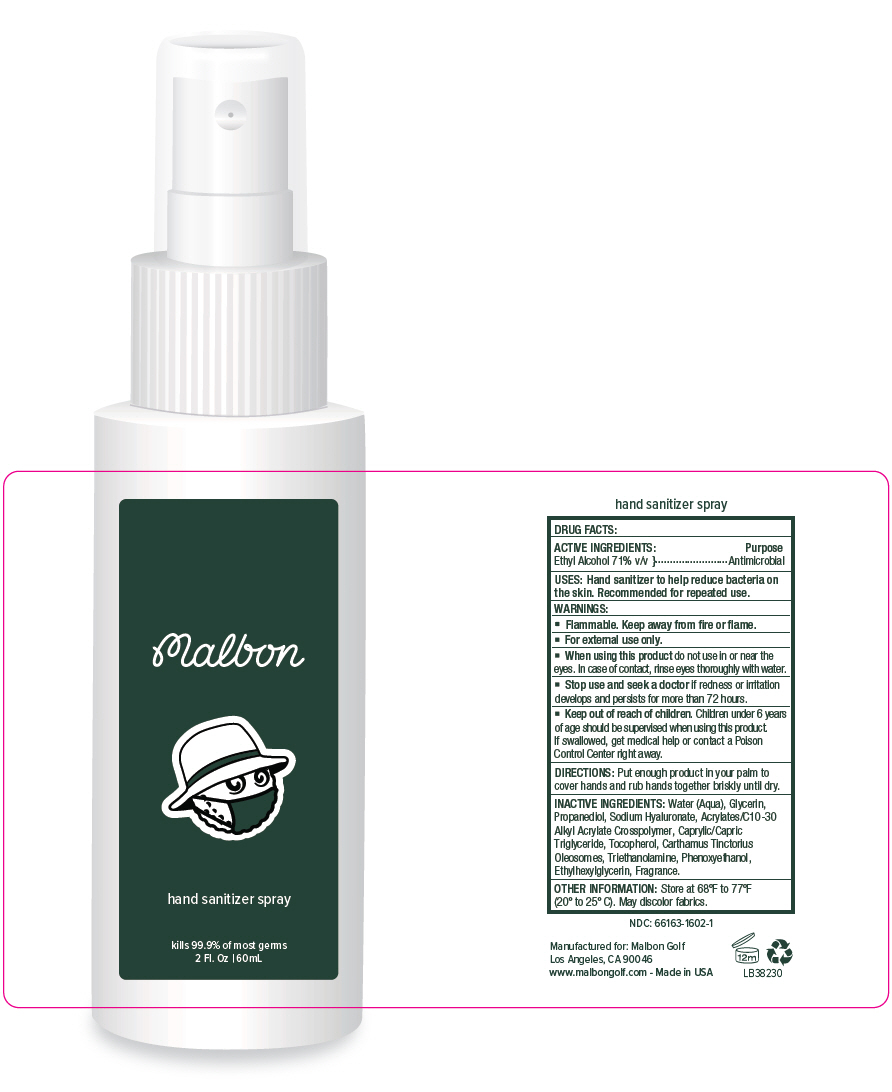 DRUG LABEL: Malbon - Hand Sanitizer
NDC: 66163-1602 | Form: SPRAY
Manufacturer: Cosmetic Solutions LLC
Category: otc | Type: HUMAN OTC DRUG LABEL
Date: 20200520

ACTIVE INGREDIENTS: Alcohol 71 mL/100 mL
INACTIVE INGREDIENTS: Water; Glycerin; Propanediol; Hyaluronate Sodium; CARBOMER INTERPOLYMER TYPE A (ALLYL SUCROSE CROSSLINKED); Medium-Chain Triglycerides; Tocopherol; CARTHAMUS TINCTORIUS SEED OLEOSOMES; Trolamine; Phenoxyethanol; Ethylhexylglycerin

Malbon - Hand Sanitizer

DRUG FACTS:

ACTIVE INGREDIENTS

Ethyl Alcohol 71% v/v

Purpose

Antimicrobial

USES

Hand sanitizer to help reduce bacteria on the skin. Recommended for repeated use.

WARNINGS

- Flammable. Keep away from fire or flame.
- For external use only.

- When using this product do not use in or near the eyes. In case of contact, rinse eyes thoroughly with water.

- Stop use and seek a doctor if redness or irritation develops and persists for more than 72 hours.

- Keep out of reach of children. Children under 6 years of age should be supervised when using this product. If swallowed, get medical help or contact a Poison Control Center right away.

DIRECTIONS

Put enough product in your palm to cover hands and rub hands together briskly until dry.

INACTIVE INGREDIENTS

Water (Aqua), Glycerin, Propanediol, Sodium Hyaluronate, Acrylates/C10-30 Alkyl Acrylate Crosspolymer, Caprylic/Capric Triglyceride, Tocopherol, Carthamus Tinctorius Oleosomes, Triethanolamine, Phenoxyethanol, Ethylhexylglycerin, Fragrance.

OTHER INFORMATION

Store at 68°F to 77°F (20° to 25° C). May discolor fabrics.

PRINCIPAL DISPLAY PANEL - 60 mL Bottle Label

Malbon

hand sanitizer spray

kills 99.9% of most germs
2 Fl. Oz | 60mL